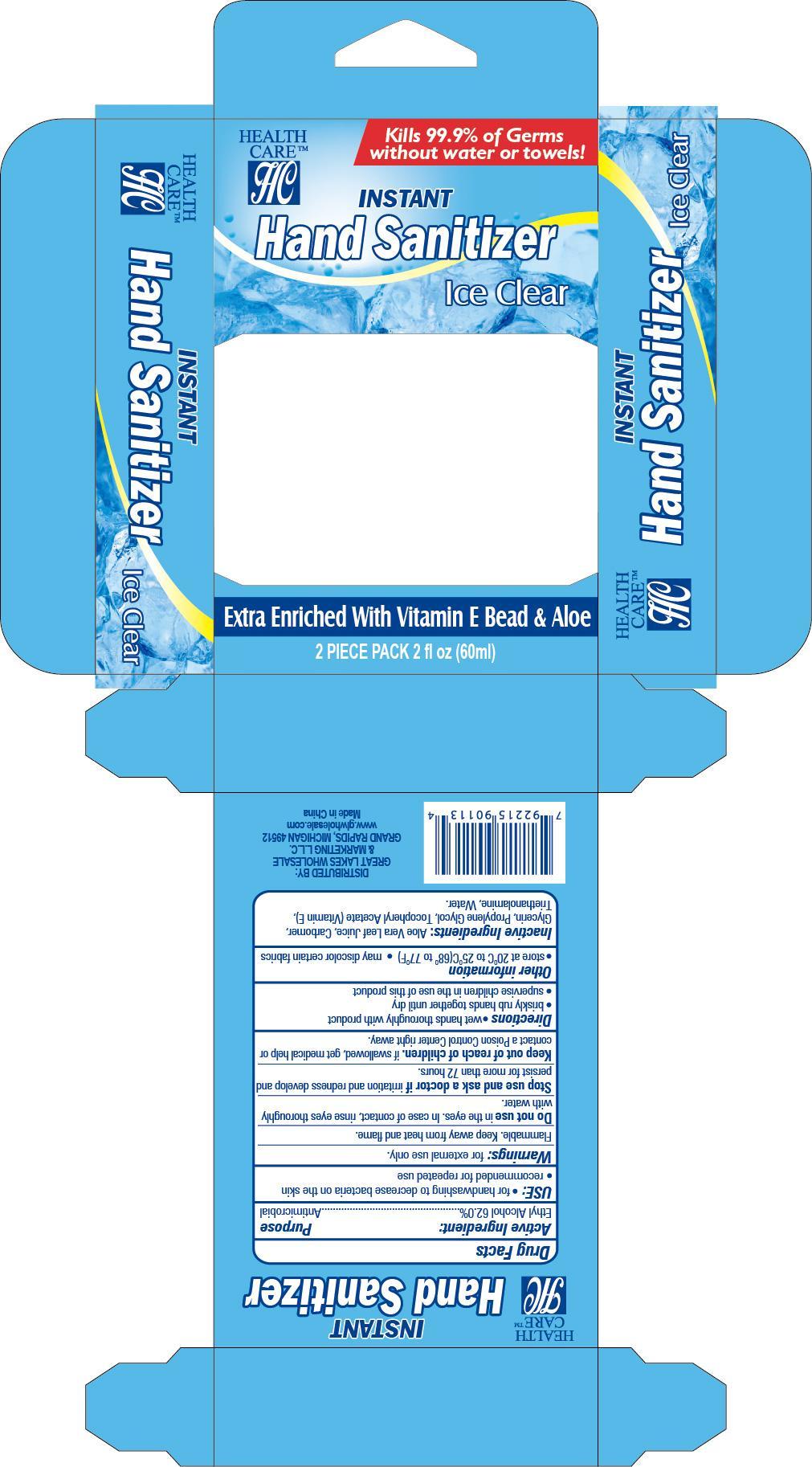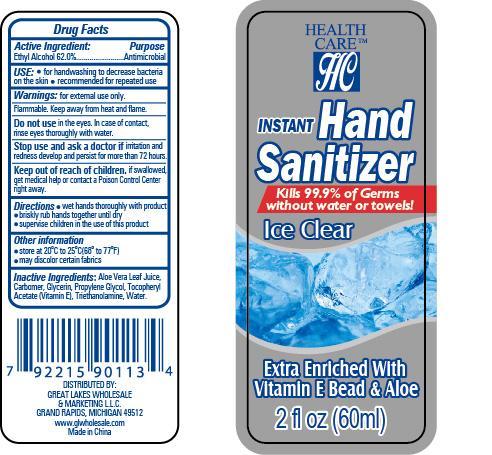 DRUG LABEL: Instant Hand Sanitizer - Ice Clear
NDC: 57337-013 | Form: GEL
Manufacturer: Rejoice International, Inc.
Category: otc | Type: HUMAN OTC DRUG LABEL
Date: 20240228

ACTIVE INGREDIENTS: ALCOHOL 37 mL/60 mL
INACTIVE INGREDIENTS: ALOE VERA LEAF; CARBOMER HOMOPOLYMER TYPE B; GLYCERIN; PROPYLENE GLYCOL; .ALPHA.-TOCOPHEROL ACETATE; TROLAMINE; WATER

Instant Hand Sanitizer - Ice Clear

Active Ingredient Purpose

Ethyl Alcohol 62.0%......................Antimicrobial

PURPOSE

Health Care Instant Hand Sanitizer - Ice Clear - Extra Enriched with Vitamin E Bead & Aloe

Kills 99.9% of Germs without water or towels!

Keep out of reach of children. If swallowed, get medical help or contact a Poison Control Center right away.

USE:

- for handwashing to decrease bacteria on the skin
- recommended for repeated use

Warnings:

for external use only.

Flammable. Keep away from heat and flame.

Do not use in the eyes. In case of contact, rinse eyes thoroughly with water.

Stop use and ask a doctor if irritation and redness develop and persist for more than 72 hours.

Directions:

- wet hands thoroughly with product
- briskly rub hands together until dry
- supervise children in the use of this product

Inactive ingredients:

aloe vera leaf juice, carbomer, glycerin, propylene glycol, tocopheryl acetate (vitamin E), triethanolamine, water.

Other information:

- store at 20oC to 25oC (68o to 77oF)
- may discolor certain fabrics